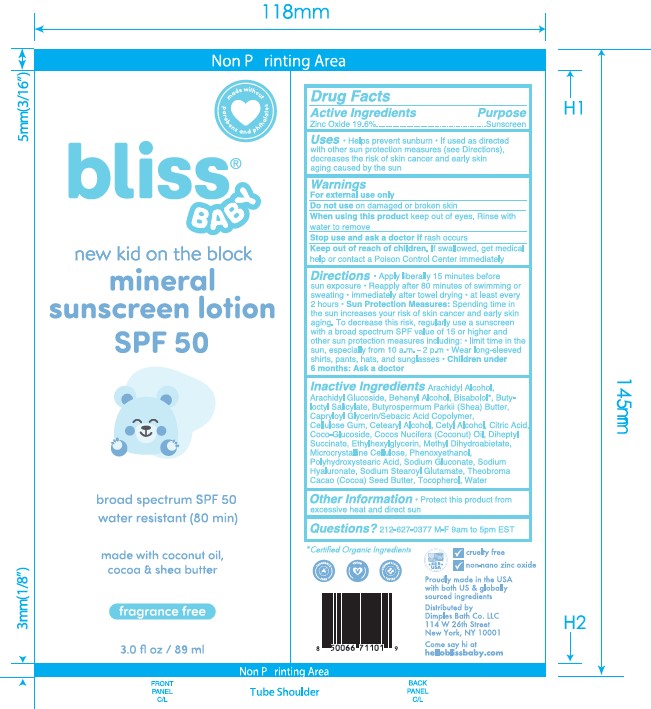 DRUG LABEL: New Kid on the Block
NDC: 84568-552 | Form: LOTION
Manufacturer: Dimples Bath Co. LLC
Category: otc | Type: HUMAN OTC DRUG LABEL
Date: 20250106

ACTIVE INGREDIENTS: ZINC OXIDE 20 g/100 g
INACTIVE INGREDIENTS: CELLULOSE GUM 0.144 g/100 g; ARACHIDYL GLUCOSIDE 0.27 g/100 g; ARACHIDYL ALCOHOL 0.99 g/100 g; POLYHYDROXYSTEARIC ACID (2300 MW) 0.1 g/100 g; BUTYLOCTYL SALICYLATE 5 g/100 g; SODIUM HYALURONATE 0.2 g/100 g; SODIUM STEAROYL GLUTAMATE 1.3 g/100 g; METHYL DIHYDROABIETATE 3 g/100 g; BUTYROSPERMUM PARKII (SHEA) BUTTER 2.1 g/100 g; TOCOPHEROL 0.1425 g/100 g; BETA-SITOSTEROL 0.075 g/100 g; CETEARYL ALCOHOL 1.3 g/100 g; CITRIC ACID 0.2 g/100 g; ETHYLHEXYLGLYCERIN 0.1 g/100 g; COCOS NUCIFERA (COCONUT) OIL 8 g/100 g; MICROCRYSTALLINE CELLULOSE 1.056 g/100 g; SQUALENE 0.0375 g/100 g; THEOBROMA CACAO (COCOA) SEED BUTTER 0.8 g/100 g; SODIUM GLUCONATE 0.2 g/100 g; BISABOLOL 0.3 g/100 g; HELIANTHUS ANNUUS (SUNFLOWER) SEED OIL 0.495 g/100 g; COCO-GLUCOSIDE 0.7 g/100 g; BEHENYL ALCOHOL 0.54 g/100 g; CAPRYLOYL GLYCERIN/SEBACIC ACID COPOLYMER (2000 MPA.S) 1.8 g/100 g; WATER 46.3 g/100 g; PHENOXYETHANOL 0.9 g/100 g; DIHEPTYL SUCCINATE 3.2 g/100 g; CETYL ALCOHOL 0.75 g/100 g

SPF 50 Lotion

ACTIVE INGREDIENT

Zinc Oxide 19.6%

PURPOSE

Sunscreen

Uses

Helps prevent sunburn. If used as directed with other sun protection measured (see Directions), decreases the risk of skin cancer and early skin aging caused by the sun

WARNINGS

For external use only

Do not use on damaged or broken skin

When using this product keep out of eyes. Rinse with water to remove

Stop use and ask a doctor if rash occurs

KEEP OUT OF REACH OF CHILDREN

If swallowed, get medical help or contact a Poison Control Center immediately

Directions

Directions • Apply liberally 15 minutes before sun exposure • Reapply after 80 minutes of swimming or sweating • Immediately after towel drying at least every 2 hours • Sun Protection Measures Spending time in the sun increases your risk of skin cancer and early skin aging. To decrease this risk, regularly use a sunscreen with a broad spectrum SPF value of 15 or higher and other sun protecting measures including • Limit time in the sun, especially from 1Oam - 2pm Wear long-sleeved shirts, pants, hats, and sunglasses • Children under 6 months Ask a doctor

INACTIVE INGREDIENT

Arachidyl Alcohol, Arachidyl Glucoside, Behenyl Alcohol, Bisabolol, Butyloctyl Salicylate, Butyrospermum Parkii (Shea) Butter, , Capryloyl Glycerin/Sebacic Acid Copolymer, Cellulose Gum, Cetearyl Alcohol, Cetyl Alcohol, Citric Acid, Coco-Glucoside, Cocos Nucifera (Coconut) OiI, Diheptyl Succinate, Ethylhexlglycerin, Methyl Dihydroabietate, Microcrystalline Cellulose, Phenoxyethanol, Polyhydroxystearic Acid, Sodium Gluconate, Sodium Hyaluronate, Sodium Stearoyl Glutamate, Theobroma Cacao (Cocoa) Seed Butter*, Tocopherol, Water

OTHER SAFETY INFORMATION

Protect this product from excessive hear and direct sun

QUESTIONS

212-627-0377 M-F 9am to 5pm EST